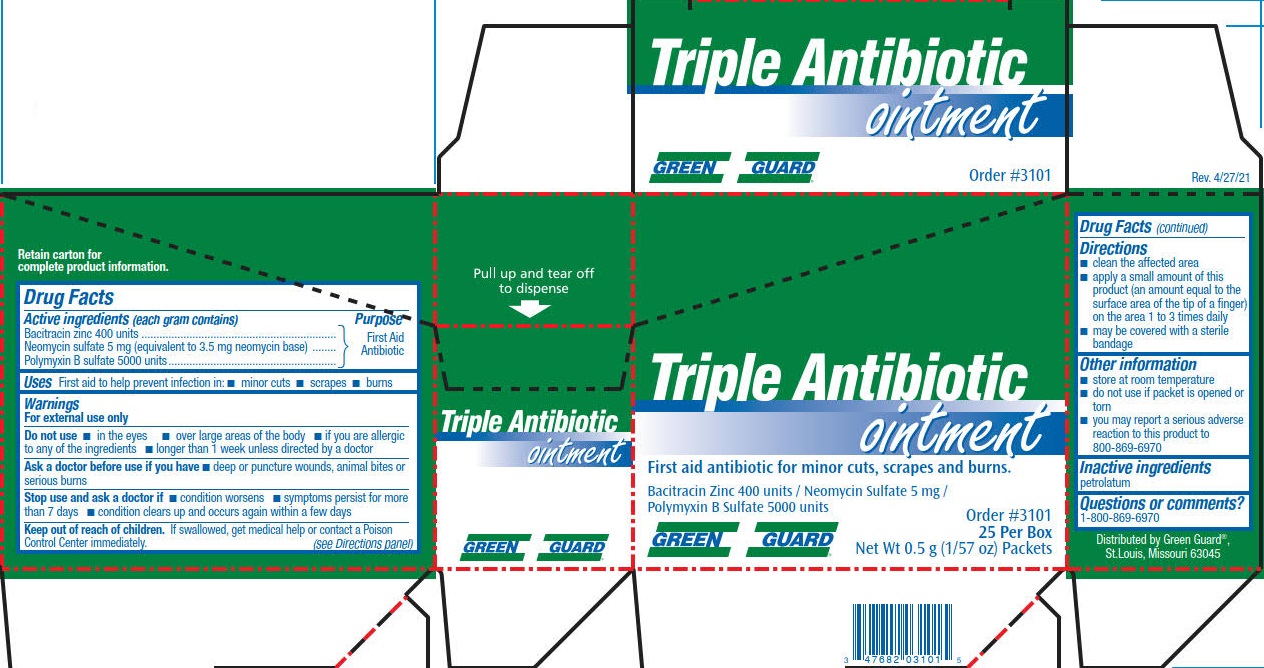 DRUG LABEL: Green Guard Triple Antibiotic
NDC: 47682-393 | Form: OINTMENT
Manufacturer: Unifirst First Aid Corporation
Category: otc | Type: HUMAN OTC DRUG LABEL
Date: 20240117

ACTIVE INGREDIENTS: POLYMYXIN B SULFATE 5000 [USP'U]/1 g; NEOMYCIN SULFATE 3.5 mg/1 g; BACITRACIN ZINC 400 [USP'U]/1 g
INACTIVE INGREDIENTS: PETROLATUM

Green Guard Triple Antibiotic Ointment

Drug Facts

Active ingredients (each gram contains)

Bacitracin zinc 400 units

Neomycin sulfate 5 mg (equivalent to 3.5 mg neomycin base)

Polymyxin B sulfate 5000 units

Purpose

First Aid Antibiotic

First Aid Antibiotic

First Aid Antibiotic

Uses

First aid to help prevent infection in:

- minor cuts
- scrapes
- burns

Warnings

For external use only

Do not use

- in the eyes
- over large areas of the body
- if you are allergic to any of the ingredients
- longer than 1 week unless directed by a doctor

Ask a doctor before use if you have

- deep or puncture wounds, animal bites or serious burns

Stop use and ask a doctor if

- condition worsens
- symptoms persist for more than 7 days
- condition clears up and occurs again within a few days

Keep out of reach of children. If swallowed, get medical help or contact a Poison Control Center immediately.

Directions

- clean the affected area
- apply a small amount of this product (an amount equal to the surface area of the tip of a finger) on the area 1 to 3 times daily
- may be covered with a sterile bandage

Other information

- store at room temperature
- tamper evident. Do not use if packet is opened or torn
- you may report a serious adverse reaction to this product to 1- 800-869-6970

Inactive ingredients petrolatum

Questions or comments? 1-800-869-6970

PACKAGE LABEL

Green Guard®

Triple Antibiotic Ointment

First aid antibiotic for minor cuts, scrapes and burns.

Bacitracin Zinc 400 units/ Neomycin Sulfate 5 mg / Polymyxin B Sulfate 5000 units

Order #3101

25 Per Box

Net Wt 0.5 g (1/57 oz) Packets